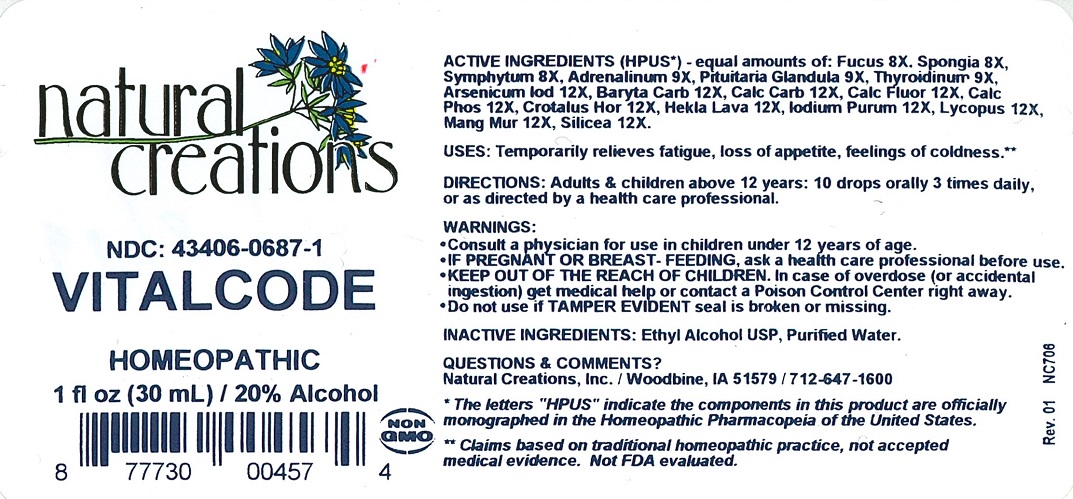 DRUG LABEL: Vitalcode
NDC: 43406-0687 | Form: LIQUID
Manufacturer: Natural Creations, Inc
Category: homeopathic | Type: HUMAN OTC DRUG LABEL
Date: 20181221

ACTIVE INGREDIENTS: FUCUS VESICULOSUS 8 [hp_X]/1 mL; SPONGIA OFFICINALIS SKELETON, ROASTED 8 [hp_X]/1 mL; COMFREY ROOT 8 [hp_X]/1 mL; EPINEPHRINE 9 [hp_X]/1 mL; SUS SCROFA PITUITARY GLAND, POSTERIOR 9 [hp_X]/1 mL; THYROID, PORCINE 9 [hp_X]/1 mL; ARSENIC TRIIODIDE 12 [hp_X]/1 mL; BARIUM CARBONATE 12 [hp_X]/1 mL; OYSTER SHELL CALCIUM CARBONATE, CRUDE 12 [hp_X]/1 mL; CALCIUM FLUORIDE 12 [hp_X]/1 mL; TRIBASIC CALCIUM PHOSPHATE 12 [hp_X]/1 mL; CROTALUS HORRIDUS HORRIDUS VENOM 12 [hp_X]/1 mL; HEKLA LAVA 12 [hp_X]/1 mL; IODINE 12 [hp_X]/1 mL; LYCOPUS VIRGINICUS WHOLE 12 [hp_X]/1 mL; MANGANESE CHLORIDE 12 [hp_X]/1 mL; SILICON DIOXIDE 12 [hp_X]/1 mL
INACTIVE INGREDIENTS: ALCOHOL; WATER

Vitalcode

ACTIVE INGREDIENT

ACTIVE INGREDIENTS (*HPUS) - equal amounts of: Fucus 8X, Spongia 8X, Symphytum 8X, Adrenalinum 9X, Pituitaria Glandula 9X, Thyroidinum 9X, Arsenicum Iod 12X, Baryta Carb 12X, Calc Carb 12X, Calc Fluor 12X, Calc Phos 12X, Crotalus Hor 12X, Hekla Lava 12X, Iodium Purum 12X, Lycopus 12X, Mang Mur 12X, Silicea 12X

INDICATIONS AND USAGE

USES: Temporarily relieves fatigue, loss of appetite, feeling of coldness.**

PURPOSE

USES: Temporarily relieves fatigue, loss of appetite, feeling of coldness.**

DOSAGE AND ADMINISTRATION

DIRECTIONS: Adults & children above 12 years: 10 drops orally 3 times daily, or as directed by a health care professional.

KEEP OUT OF REACH OF CHILDREN

KEEP OUT OF THE REACH OF CHILDREN. In case of overdose (or accidental ingestion) get medical help or contact a Poison Control Center right away.

WARNINGS:

- Consult a physician for use in children under 12 years of age.
- IF PREGNANT OR BREAST-FEEDING, ask a health care professional before use.
- KEEP OUT OF THE REACH OF CHILDREN. In case of overdose (or accidental ingestion) get medical help or contact a Poison Control Center right away.
- Do not use if TAMPER EVIDENT seal is broken or missing.

INACTIVE INGREDIENTS: Ethyl Alcohol USP, Purified Water.

QUESTIONS & COMMENTS?

Natural Creations, Inc. / Woodbine, IA 51579 / 712-647-1600

REFERENCES

*The letters "HPUS" indicate the components in this product are officially monographed in the Homeopathic Pharmacopeia of the United States.

**Claims based on traditional homeopathic practice, not accepted medical evidence. Not FDA evaluated.

PACKAGE LABEL

NDC:43406-0687-1

Vitalcode

HOMEOPATHIC

1 fl oz (30mL) / 20% Alcohol